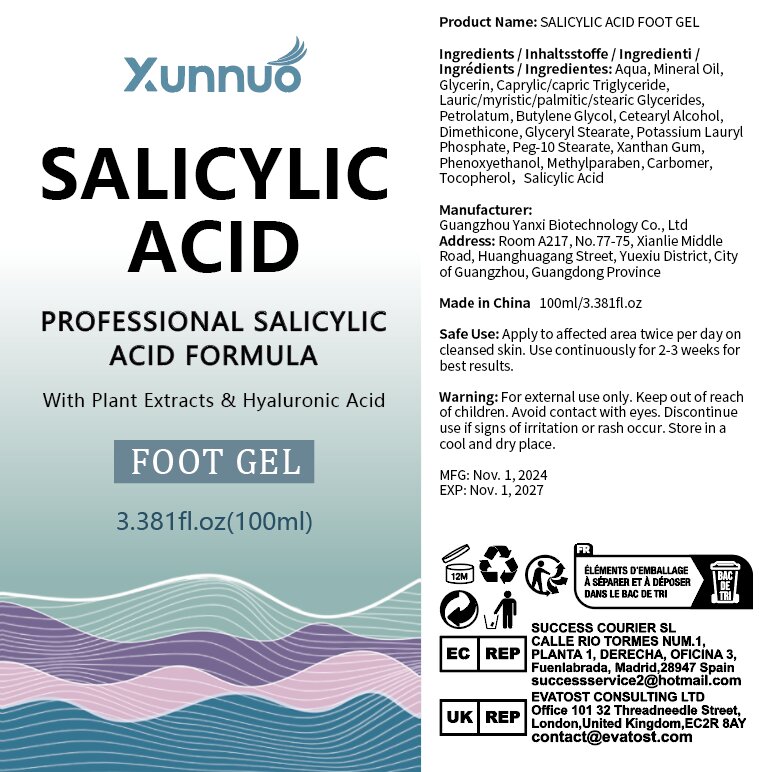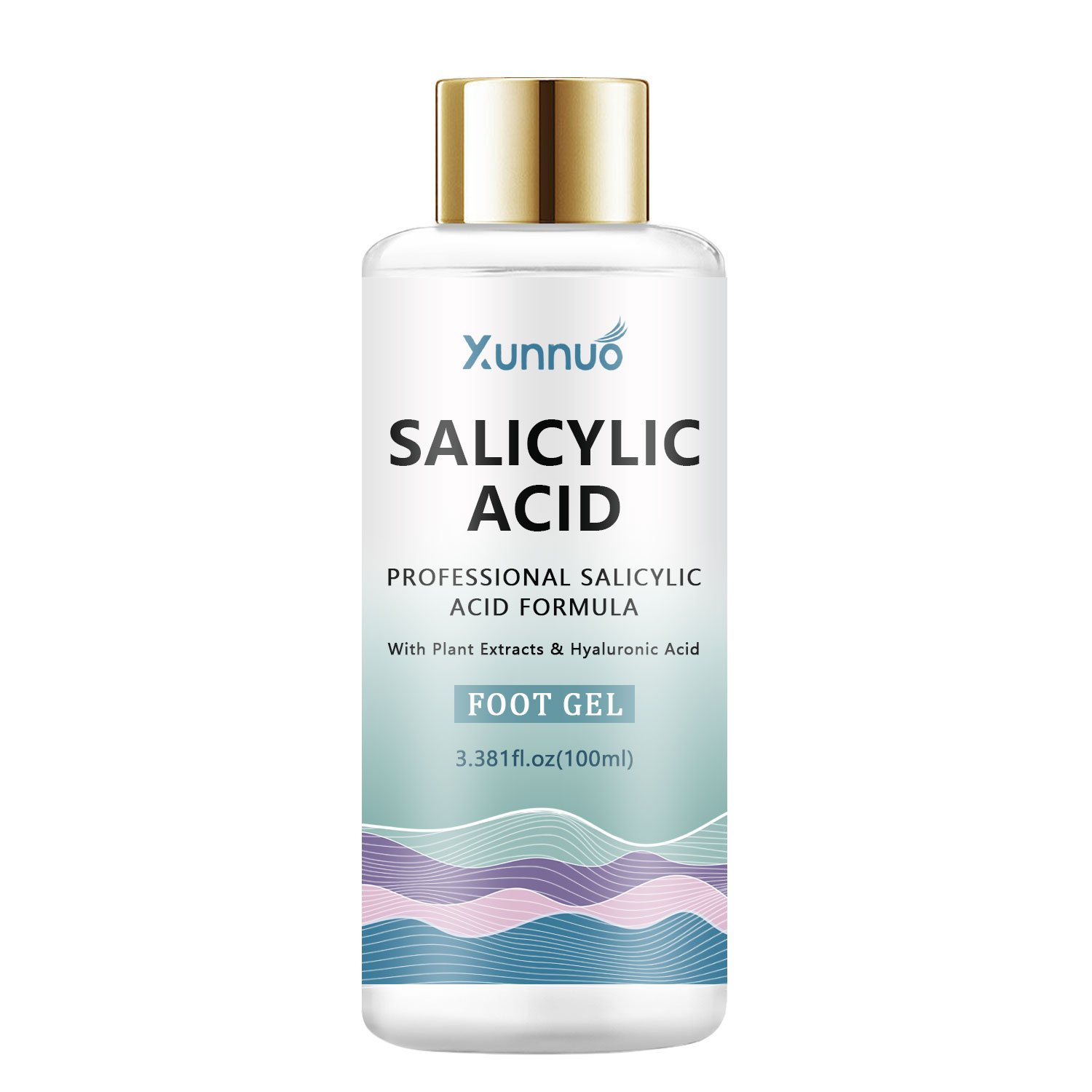 DRUG LABEL: Salicylic acid foot gel
NDC: 84025-321 | Form: GEL
Manufacturer: Guangzhou Yanxi Biotechnology Co., Ltd
Category: otc | Type: HUMAN OTC DRUG LABEL
Date: 20250108

ACTIVE INGREDIENTS: MINERAL OIL 5 mg/100 mL; GLYCERIN 3 mg/100 mL
INACTIVE INGREDIENTS: WATER

DOSAGE AND ADMINISTRATION

USE AS A NORMAL FOOT GEL

WARNINGS

keep out of children

INACTIVE INGREDIENT

Aqua

INDICATIONS AND USAGE

For daily foot care

keep out of children

PURPOSE

Foot moisturizing and hydration